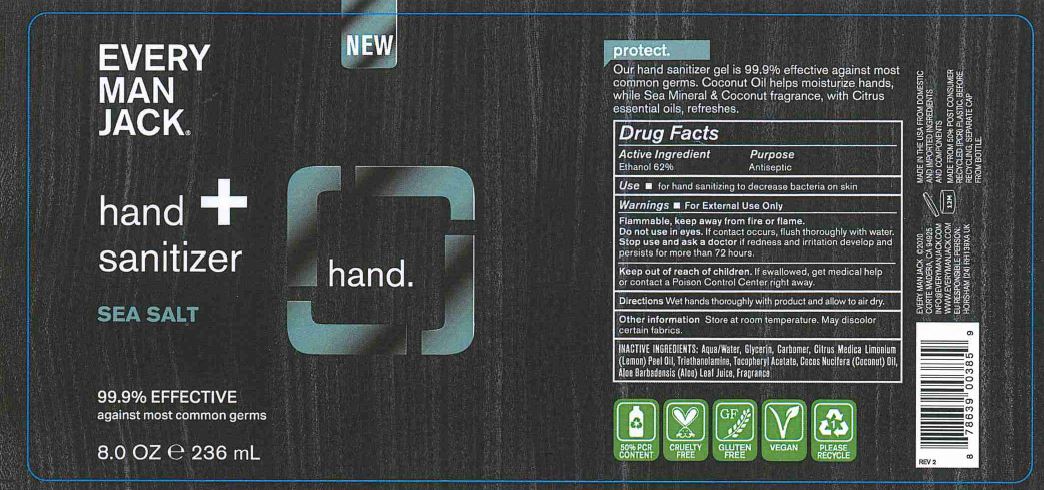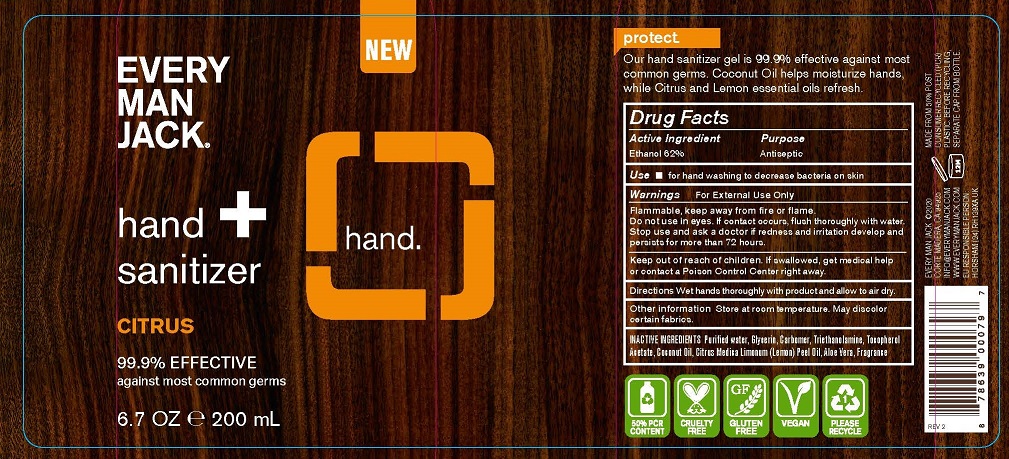 DRUG LABEL: EVERY MAN JACK - HAND SANITIZER
NDC: 57934-5014 | Form: GEL
Manufacturer: EVERY MAN JACK
Category: otc | Type: HUMAN OTC DRUG LABEL
Date: 20211227

ACTIVE INGREDIENTS: ALCOHOL 62 mL/100 mL
INACTIVE INGREDIENTS: WATER; GLYCERIN; CARBOMER HOMOPOLYMER, UNSPECIFIED TYPE; TROLAMINE; .ALPHA.-TOCOPHEROL ACETATE; COCONUT OIL; LEMON OIL; ALOE VERA LEAF

EVERY MAN JACK - HAND SANITIZER GEL (62% ETHANOL) - 57934-5014

ACTIVE INGREDIENT

ETHYL ALCOHOL 62%

PURPOSE

ANTISEPTIC

USES

FOR HAND WASHING TO DECREASE BACTERIA ON SKIN.

WARNINGS

FOR EXTERNAL USE ONLY.

FLAMMABLE, KEEP AWAY FROM FIRE OR FLAME.

DO NOT USE IN EYES. IF CONTACT OCCURS, FLUSH THOROUGHLY WITH WATER. STOP USE AND ASK A DOCTOR IF REDNESS AND IRRITATION DEVELOP AND PERSISTS FOR MORE THAN 72 HOURS.

KEEP OUT OF REACH OF CHILDREN. IF SWALLOWED, GET MEDICAL HELP OR CONTACT A POISON CONTROL CENTER RIGHT AWAY.

DIRECTIONS

WET HANDS THOROUGHLY WITH PRODUCT AND ALLOW TO AIR DRY.

OTHER INFORMATION

STORE AT ROOM TEMPERATURE. MAY DISCOLOR CERTAIN FABRICS.

INACTIVE INGREDIENTS

CITRUS: PURIFIED WATER, GLYCERIN, CARBOMER, TRIETHANOLAMINE, TOCOPHERYL ACETATE, COCONUT OIL, CITRUS MEDICA (LEMON) PEEL OIL, ALOE VERA, FRAGRANCE

SEA SALT: AQUA/WATER, GLYCERIN, CARBOMER, CITRUS MEDICA LIMONUM (LEMON) PEEL OIL, TRIETHANOLAMINE, TOCOPHERYL ACETATE, COCUS NUCIFERA (COCONUT) OIL, ALOE BARBADENSIS (ALOE) LEAF JUICE, FRAGRANCE